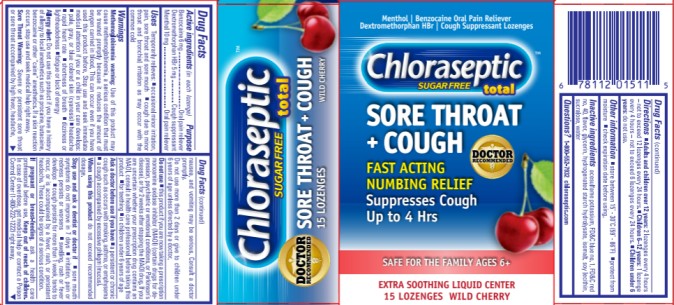 DRUG LABEL: Chloraseptic Total Sore Throat and Cough, Sugar Free
NDC: 67172-015 | Form: LOZENGE
Manufacturer: Prestige Brands Holdings, Inc.
Category: otc | Type: HUMAN OTC DRUG LABEL
Date: 20251023

ACTIVE INGREDIENTS: MENTHOL 10 mg/1 1; BENZOCAINE 6 mg/1 1; DEXTROMETHORPHAN HYDROBROMIDE 5 mg/1 1
INACTIVE INGREDIENTS: ACESULFAME POTASSIUM; FD&C BLUE NO. 1; FD&C RED NO. 40; GLYCERIN; HYDROGENATED STARCH HYDROLYSATE; LECITHIN, SOYBEAN; SUCRALOSE; WATER

Chloraseptic Sugar Free Lozenges

Drug Facts

Active Ingredients

(in each lozenge)

Benzocaine 6 mg

Purpose

Oral pain reliever

Active Ingredients

(in each lozenge)

Dextromethorphan HBr 5 mg

Purpose

Cough Suppressant

Active Ingredients

(in each lozenge)

Menthol 10 mg

Purpose

Oral pain reliever

Uses

Temporarily relieves

- occasional minor irritation, pain, sore throat and sore mouth
- cough due to minor throat and bronchial irritation as may occur with the common cold

Warnings

Methemoglobinemia warning:

Use of this product may cause methemoglobinemia, a serious condition that must be treated promptly because it reduces the amount of oxygen carried in blood. This can occur even if you have used this product before. Stop use and seek immediate medical attention if you or a child in your care develops:

∙ pale, gray, or blue colored skin (cyanosis)

∙ headache

∙ rapid heart rate

∙ shortness of breath

∙ dizziness or lightheadedness

∙ fatigue or lack of energy

Allergy Alert: Do not use this product if you have a history of allergy to local anesthetics such as procaine, butacaine, benzocaine or other “caine” anesthetics. If a skin reaction occurs, stop use and seek medical help right away.

Sore Throat Warning: Severe or persistent sore throat or sore throat accompanied by high fever, headache, nausea, and vomiting may be serious. Consult doctor promptly. Do not use more than 2 days or administer to children under 6 years of age unless directed by a doctor.

Do not use

- this product if you are now taking a prescription monoamine oxidase inhibitor (MAOI) (certain drugs for depression, psychiatric or emotional conditions, or Parkinson’s disease), or for 2 weeks after stopping the MAOI drug. If you are uncertain whether your prescription drug contains an MAOI, consult a health care professional before taking this product.
- for teething
- in children under 6 years of age

Ask a doctor before use if you have

- a persistent or chronic cough such as occurs with smoking, asthma, or emphysema
- a cough accompanied by excessive phlegm (mucus)

When using this product

do not exceed recommended dosage.

Stop use and ask a dentist or doctor if:

- sore mouth symptoms do not improve in 7 days
- irritation, pain or redness persists or worsens
- swelling, rash or fever develops
- cough persists for more than 1 week, tends to recur, or is accompanied by a high fever, rash, or persistent headache. These could be symptoms of a serious condition.

If pregnant or breast-feeding,

ask a health care professional before use.

Keep out of reach of children.

In case of overdose, get medical help or contact a Poison Control Center (1-800-222-1222) right away.

Directions

- Adults and children over 12 years of age: 2 lozenges every 4 hours – not to exceed 12 lozenges every 24 hours.
- Children 6-12 years of age: 1 lozenge every 4 hours – not to exceed 6 lozenges every 24 hours.
- Children under 6 years of age: do not use.

Other Information

- Store between 15ºC - 30º (59ºF - 86ºF) .
- Protect from moisture.
- Check expiration date before using.

Inactive Ingredients

Acesulfame Potassium, FD&C Blue no. 1, FD&C Red no. 40, Flavor, Glycerine, Hydrogenated Starch Hydrolysate, Isomalt, Soy Lecithin, Sucralose, Water

Questions?

1-800-552-7932 Chloraseptic.com

PRINCIPAL DISPLAY PANEL

Chloraseptic® Total Sugar Free
SORE THROAT + COUGH Lozenges
Benzocaine / Menthol / Oral Anesthetic/Analgesic
Dextromethorphan HBr /Cough Suppressant
Wild Cherry|15 lozenges